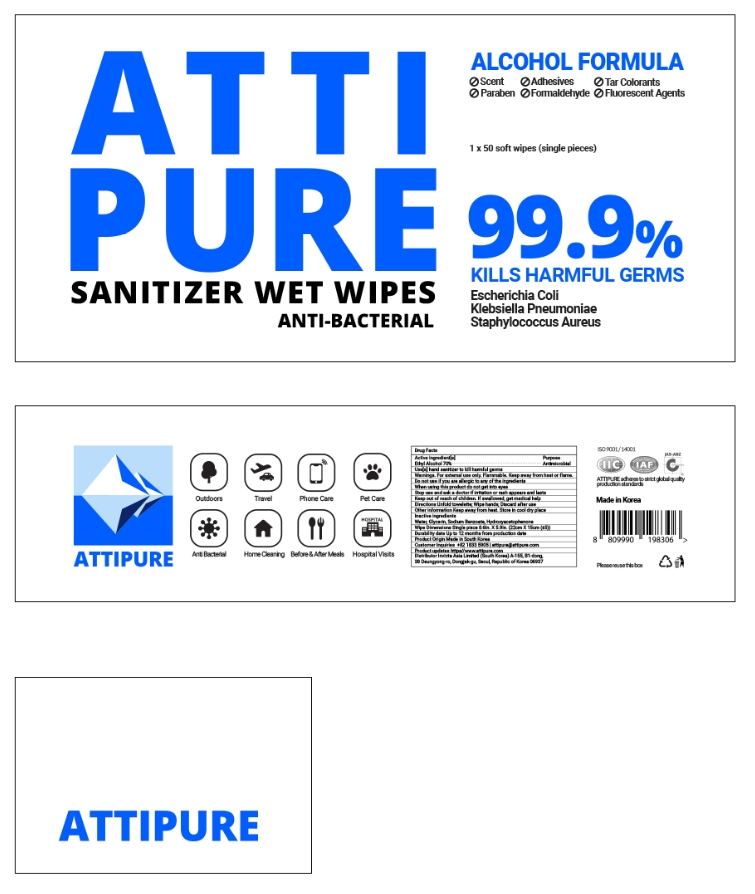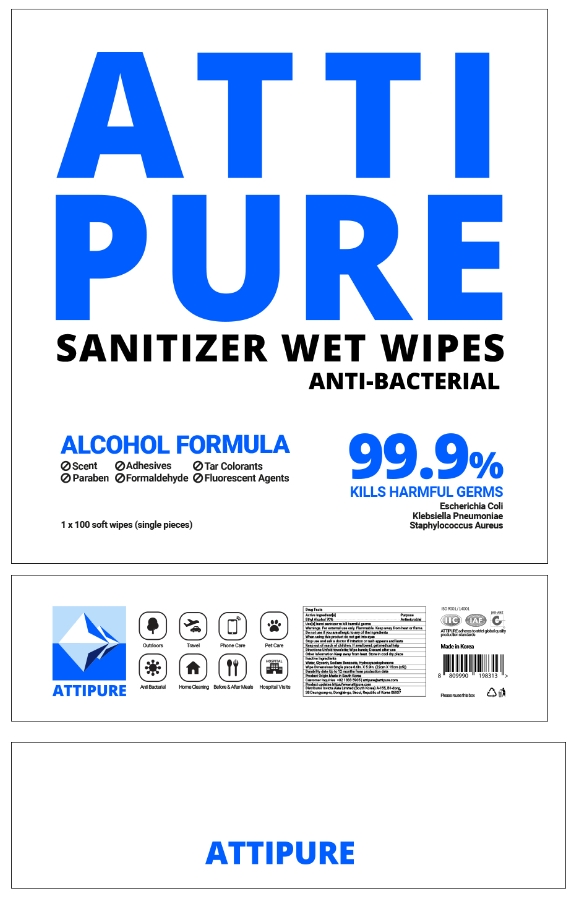 DRUG LABEL: ATTIPURE SANITIZER WET WIPES
NDC: 76709-202 | Form: LIQUID
Manufacturer: INVICTA ASIA CO., LTD
Category: otc | Type: HUMAN OTC DRUG LABEL
Date: 20200509

ACTIVE INGREDIENTS: ALCOHOL 70 g/100 g
INACTIVE INGREDIENTS: WATER; GLYCERIN; SODIUM BENZOATE; HYDROXYACETOPHENONE

Active ingredient[s]

Ethyl Alcohol 70%

Purpose

Antimicrobial

Use[s]

hand sanitizer to kill harmful germs

Warnings

For external use only. Flammable. Keep away from heat or flame.

Do not use

if you are allergic to any of the ingredients

When using this product

do not get into eyes

Stop use and ask a doctor

if irritation or rash appears and lasts

Keep out of reach of children

If swallowed, get medical help

Directions

Unfold towelette; Wipe hands; Discard after use

Other information

Keep away from heat. Store in cool dry place

Inactive ingredients

Water, Glycerin, Sodium Benzoate, Hydroxyacetophenone